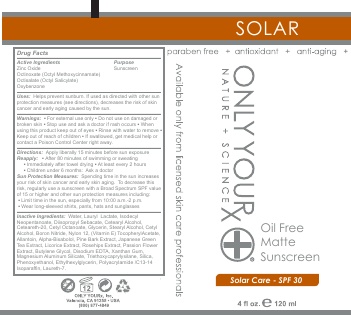 DRUG LABEL: Oil Free Matte Sunscreen SPF 30, - Zinc Oxide, Octinoxate, Octisalate, Oxybenzone
NDC: 70367-007 | Form: LOTION
Manufacturer: Only Yourx, Inc.
Category: otc | Type: HUMAN OTC DRUG LABEL
Date: 20200123

ACTIVE INGREDIENTS: OCTINOXATE 6.75 g/100 mL; OCTISALATE 2.7 g/100 mL; OXYBENZONE 4.5 g/100 mL; ZINC OXIDE 7.2 g/100 mL
INACTIVE INGREDIENTS: PHENOXYETHANOL; ETHYLHEXYLGLYCERIN; GREEN TEA LEAF; LICORICE; MAGNESIUM ALUMINUM SILICATE; WATER; LAURYL LACTATE; GLYCERIN; CETYL ALCOHOL; XANTHAN GUM; ISODECYL NEOPENTANOATE; DIISOPROPYL SEBACATE; STEARYL ALCOHOL; SQUALANE; POLYSORBATE 60

PURPOSE

Protects against UVA/UVB rays

INDICATIONS AND USAGE

Protects against skin-aging UVA/UVB rays with advanced, broad-spectrum sunscreens and powerful antioxidants. Lightweight and water-resistant, this formula won't clog pores to help prevent breakouts. Leaves a matte finish

ACTIVE INGREDIENT

Active Ingredients: Zinc Oxide, Octinoxate (Octyl Methoxycinnamate), Octisalate (Octyl Salicylate), Oxybenzone

INACTIVE INGREDIENT

SLauryl Lactate, Isodecyl Neopentanoate, Diisopropyl Sebacate, Cetearyl Alcohol, Ceteareth-20, Cetyl Octanoate, Glyerin, Stearyl Alcohol, Cetyl Alcohol, Boron Nitride, Nylon 12, Vitamin E Tocopheryl Acetate, Allantoin, Alpha-Bisabolol, Pine Bark Extract, Green Tea Extract, Licorice Extract, Rosehips Extract, Passion Flower Extract, Butylene Glycol, Disodium EDTA, Xanthan Gum, Magnesium Aluminum Silicate, Triethoxycaprylsilane, Laureth-7, Ethylhexylglycerin, Phenoxyethanol, Polyacrylamide/C13-14 Isoparaffin

DOSAGE AND ADMINISTRATION

Apply a liberal amount approximately 30 minutes prior to sun exposure. For continuous protection, reapply regularly and after swimming and/or exercising

WARNINGS

Warnings: For external use only; Do not use on damaged or broken skin; Stop use and ask a doctor if rash occurs; When using this product keep out of eyes; Rinse with water to remove

Keep out of reach of children. If swallowed get medical help or contact a Poison Control Center right away.